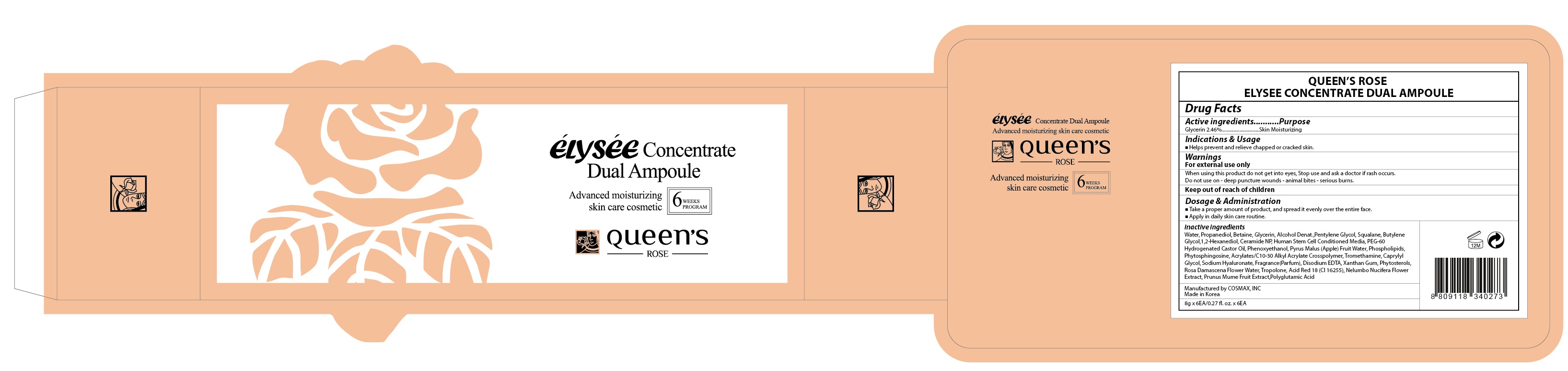 DRUG LABEL: QUEENS ROSE ELYSEE CONCEN TRATE DUAL AMPOULE
NDC: 71252-090 | Form: LIQUID
Manufacturer: Cdpharmtec Co.,ltd
Category: otc | Type: HUMAN OTC DRUG LABEL
Date: 20170324

ACTIVE INGREDIENTS: Glycerin 0.19 g/8 g
INACTIVE INGREDIENTS: Water; Propanediol

ACTIVE INGREDIENT

Active ingredients: Glycerin 2.46%

INACTIVE INGREDIENT

Inactive ingredients: Water, Propanediol, Betaine, Glycerin, Alcohol Denat.,Pentylene Glycol, Squalane, Butylene Glycol,1,2-Hexanediol, Ceramide NP, Human Stem Cell Conditioned Media, PEG-60 Hydrogenated Castor Oil, Phenoxyethanol, Pyrus Malus (Apple) Fruit Water, Phospholipids, Phytosphingosine, Acrylates/C10-30 Alkyl Acrylate Crosspolymer, Tromethamine, Caprylyl Glycol, Sodium Hyaluronate, Fragrance(Parfum), Disodium EDTA, Xanthan Gum, Phytosterols, Rosa Damascena Flower Water, Tropolone, Acid Red 18 (CI 16255), Nelumbo Nucifera Flower Extract, Prunus Mume Fruit Extract,Polyglutamic Acid

PURPOSE

Purpose: Skin Moisturizing

WARNINGS

Warnings: For external use only When using this product do not get into eyes, Stop use and ask a doctor if rash occurs. Do not use on - deep puncture wounds - animal bites - serious burns.

KEEP OUT OF REACH OF CHILDREN

INDICATIONS & USAGE

Indications & Usage: Helps prevent and relieve chapped or cracked skin.

DOSAGE & ADMINISTRATION

Dosage & Administration: - Take a proper amount of product, and spread it evenly over the entire face. - Apply in daily skin care routine.